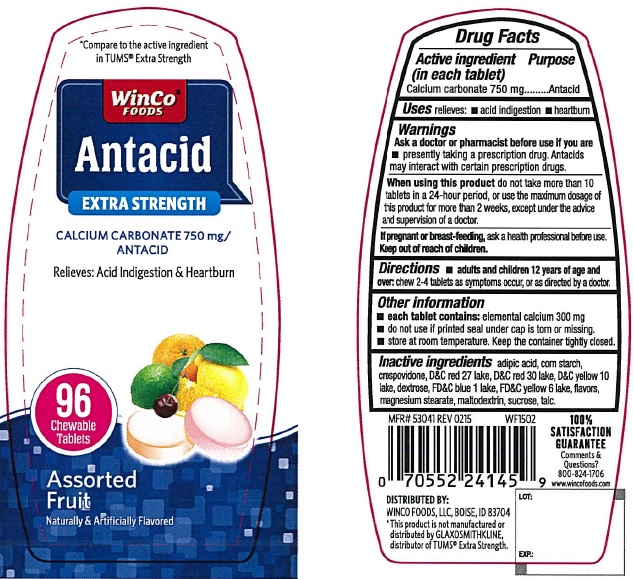 DRUG LABEL: Antacid Extra Strength Assorted Fruit
NDC: 67091-228 | Form: TABLET, CHEWABLE
Manufacturer: WinCo Foods, LLC
Category: otc | Type: HUMAN OTC DRUG LABEL
Date: 20220114

ACTIVE INGREDIENTS: CALCIUM CARBONATE 750 mg/1 1
INACTIVE INGREDIENTS: ADIPIC ACID; STARCH, CORN; CROSPOVIDONE; D&C RED NO. 27; D&C RED NO. 30; D&C YELLOW NO. 10; DEXTROSE, UNSPECIFIED FORM; FD&C BLUE NO. 1; FD&C YELLOW NO. 6; MAGNESIUM STEARATE; MALTODEXTRIN; SUCROSE; TALC

Antacid Extra Strength Assorted Fruit

Active ingredient (in each tablet)

Calcium carbonate 750 mg

Purpose

Antacid

Uses

relieves

- acid indigestion
- heartburn

Warnings

Ask a doctor or pharmacist before use if you are

taking a prescription drug. Antacids may interact with certain prescription drugs.

When using this product

do not take more than 10 tablets in a 24-hour period, or use the maximum dosage of this product for more than 2 weeks, except under the advice and supervision of a doctor.

Keep out of reach of children

Directions

- chew 2-4 tablets as symptoms occur, or as directed by a doctor.

Other information

- do not use if printed seal under cap is torn or missing.
- store at room temperature.

Inactive ingredients

adipic acid, corn starch, crospovidone, DC red 27 lake, DC red 30 lake, DC yellow 10 lake, dextrose, FDC blue 1 lake, FDC yellow 6 lake, flavors, magnesium stearate, maltodextrin, sucrose, talc

PACKAGE LABEL

*Compare to the active ingredient in TUMS® Extra Strength

Antacid Extra Strength

CALCIUM CARBONATE 750 mg / ANTACID

Relieves: Acid Indigestion & Heartburn

Assorted Fruit

Naturally & Artificially Flavored

96 Chewable Tablets